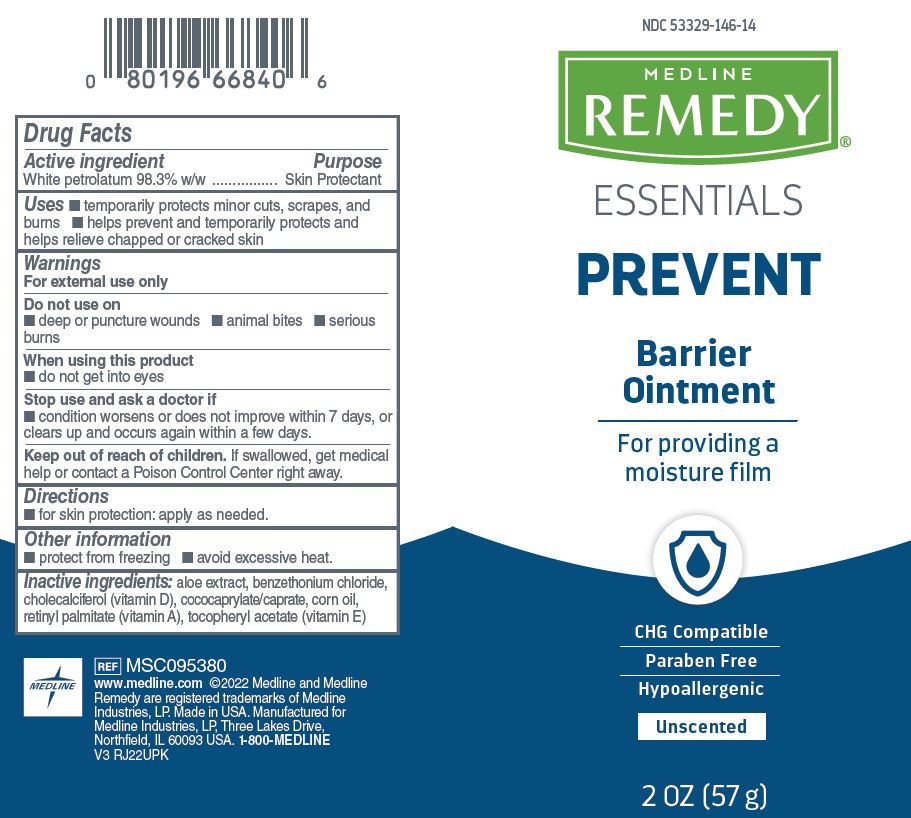 DRUG LABEL: Medline
NDC: 53329-146 | Form: OINTMENT
Manufacturer: Medline Industries, LP
Category: otc | Type: HUMAN OTC DRUG LABEL
Date: 20241203

ACTIVE INGREDIENTS: WHITE PETROLATUM 983 mg/1 g
INACTIVE INGREDIENTS: ALOE; CHOLECALCIFEROL; CORN OIL; VITAMIN A PALMITATE; ALPHA-TOCOPHEROL ACETATE; BENZETHONIUM CHLORIDE; COCO-CAPRYLATE/CAPRATE

146 Remedy Essentials Barrier Ointment

Active ingredient

White petrolatum 98.3% w/w

Purpose

Skin protectant

Uses

- temporarily protects minor cuts, scrapes, and burns
- helps prevent and temporarily protects and helps relieve chapped or cracked skin

Warnings

For external use only

Do not use on

- deep or puncture wounds
- animal bites
- serious burns

When using this product

- do not get into eyes

Stop use and ask a doctor if

- condition worsens or does not improve within 7 days, or clears up and occurs again within a few days

Keep out of reach of children.

If swallowed, get medical help or contact a Poison Control Center right away.

Directions

- for skin protection: apply as needed

Other information

- protect from freezing
- avoid excessive heat

Inactive ingredients

aloe extract, benzethonium chloride, cholecalciferol (vitamin D), cococaprylate/caprate, corn oil, retinyl palmitate (vitamin A), tocopheryl acetate (vitamin E)

Manufacturing information

Manufactured for:

Medline Industries, LP

Three Lakes Drive, Northfield, IL 60093 USA

Made in USA

www.medline.com

1-800-MEDLINE (633-5463)

REF: MSC095380

V3 Rj22UPK